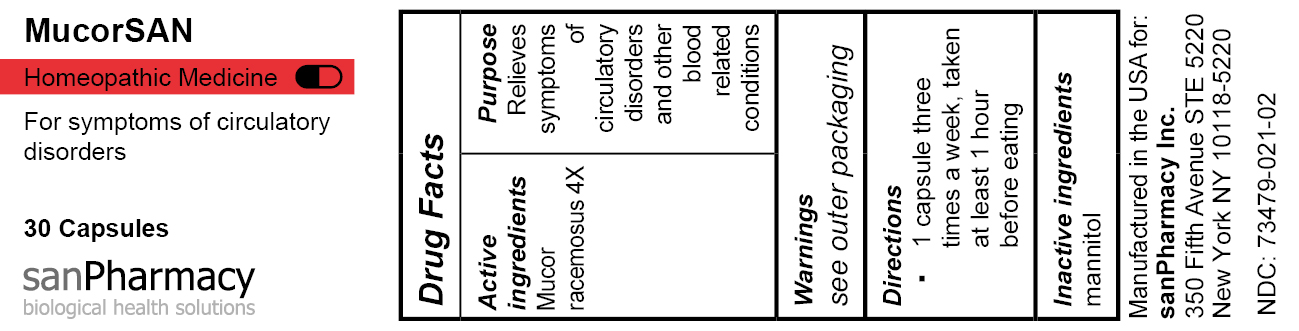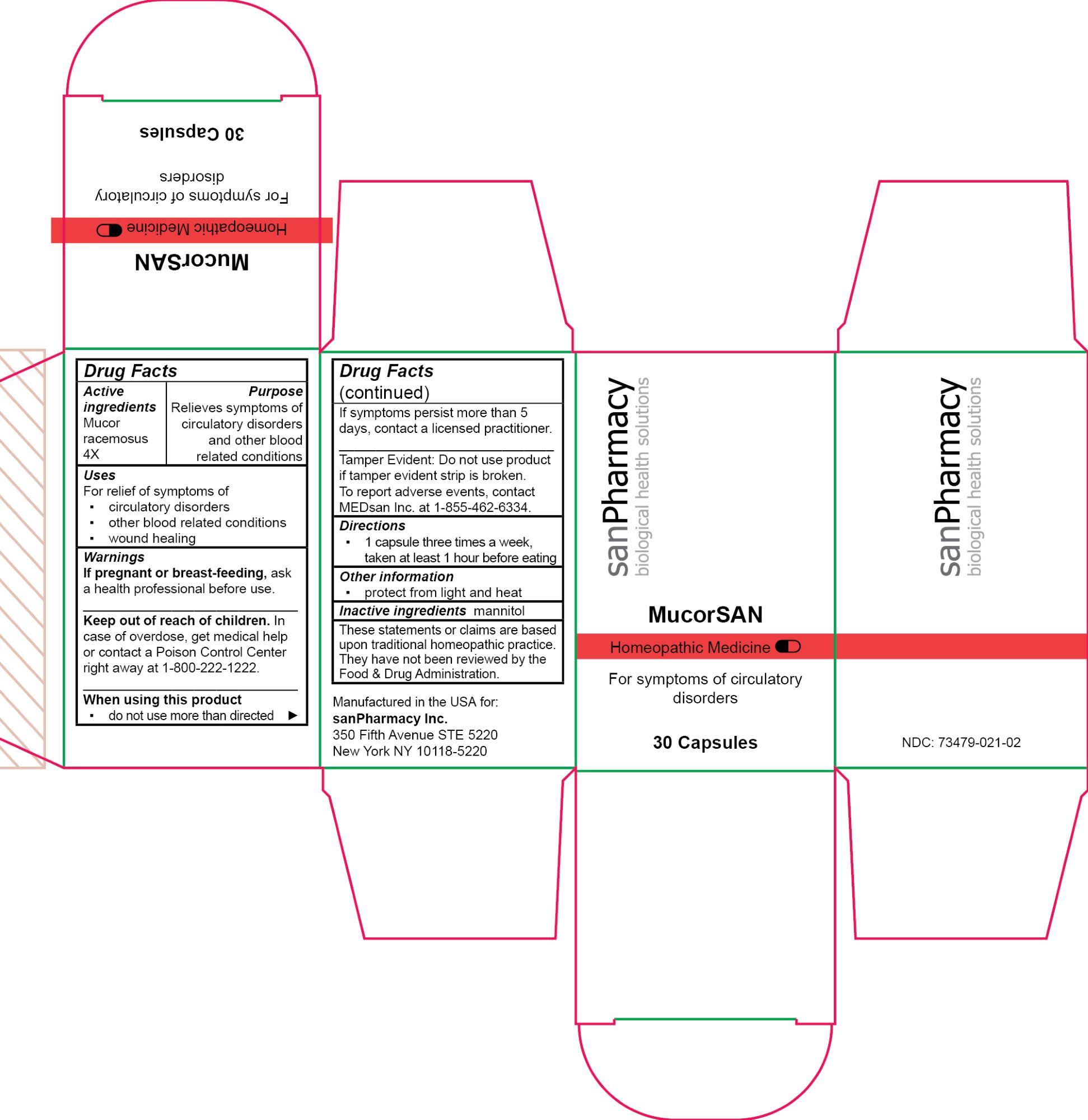 DRUG LABEL: MucorSAN
NDC: 73479-021 | Form: CAPSULE
Manufacturer: sanPharmacy Inc.
Category: homeopathic | Type: HUMAN OTC DRUG LABEL
Date: 20240425

ACTIVE INGREDIENTS: MUCOR RACEMOSUS 4 [hp_X]/1 1
INACTIVE INGREDIENTS: MANNITOL

MucorSAN Capsules

Indications

For symptoms of circulatory disorders

Purpose

Relieves symptoms of circulatory disorders and other blood related conditions

Dosage

1 capsule three times a week, taken at least 1 hour before eating

ACTIVE INGREDIENT

Mucor racemosus 4X

INACTIVE INGREDIENT

mannitol

Warnings

If pregnant or breast-feeding, ask a health professional before use.
______________________________
Keep out of reach of children. In case of overdose, get medical help or contact a Poison Control Center right away at 1-800-222-1222.
______________________________
When using this product
▪ do not use more than directed
______________________________
If symptoms persist more than 5 days, contact a licensed practitioner.
______________________________
Tamper Evident: Do not use product if tamper evident strip is broken. To report adverse events, contact MEDsan Inc. at 1-855-462-6334.

Keep out of reach of children. In case of overdose, get medical help or contact a Poison Control Center right away at 1-800-222-1222

Tamper Evident

Tamper Evident: Do not use product if tamper evident strip is broken. To report adverse events, contact MEDsan Inc. at 1-855-462-6334

Manufactured in the USA for:
sanPharmacy Inc.
350 Fifth Avenue STE 5220
New York NY 10118-5220

STORAGE AND HANDLING

protect from light and heat

Liability statement

These statements or claims are based upon traditional homeopathic practice. They have not been reviewed by the Food & Drug Administration.

PRINCIPAL DISPLAY PANEL

MucorSAN

Homeopathic Medicine

For symptoms of circulatory disorders

30 Capsules

sanPharmacy

biological health solutions